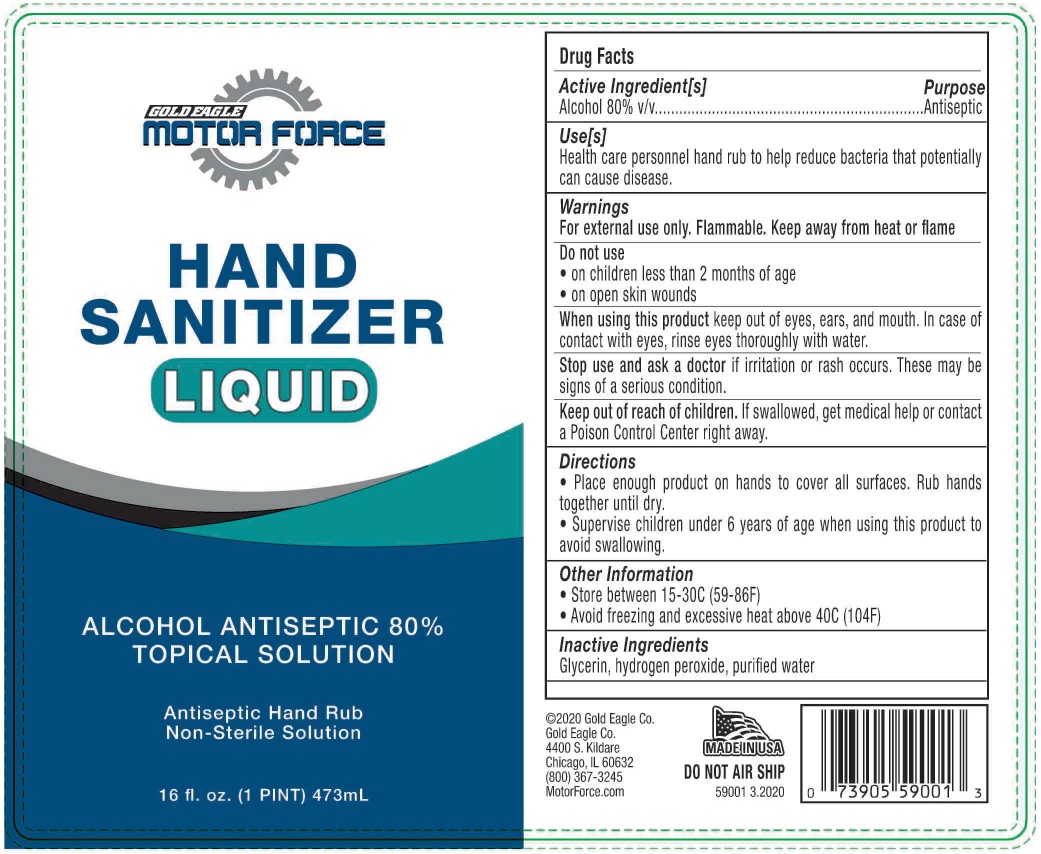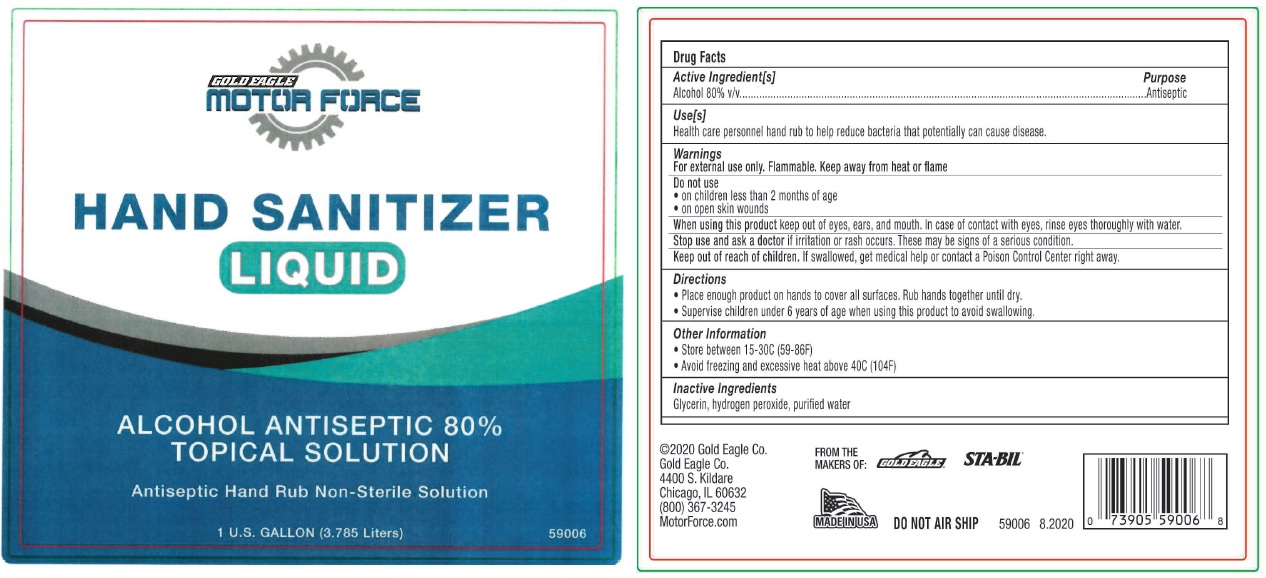 DRUG LABEL: Gold Eagle Motor Force Hand Sanitizer
NDC: 78007-113 | Form: LIQUID
Manufacturer: Gold Eagle Co.
Category: otc | Type: HUMAN OTC DRUG LABEL
Date: 20200825

ACTIVE INGREDIENTS: ALCOHOL 80 mL/100 mL
INACTIVE INGREDIENTS: GLYCERIN; HYDROGEN PEROXIDE; WATER

GOLD EAGLE MOTOR FORCE HAND SANITIZER

Active Ingredients[s]

Alcohol 80% v/v

Purpose

Antiseptic

Use[s]

Health care personnel hand rub to help reduce bacteria that potentially can cause disease.

Warnings

For external use only. keep away from heat or flame

Do not use

• on children less than 2 months of age

• on open skin wounds

When using this product keep out of eyes, ears, and mouth. In case of contact with eyes, rinse eyes thoroughly with water.

Stop use and ask a doctor if irritation or rash occurs. These may be signs of serious condition.

Keep out of reach of children. If swallowed, get medical help or contact a Poison Control Center right away.

Directions

• Place enough product on hands to cover all surfaces. Rub hands together until dry.

• Supervise children under 6 years of age when using this product to avoid swallowing.

Other Information

• Store between 15-30C (59-86F)

• Avoid freezing and excessive heat above 40C (104F)

Inactive Ingredients

Glycerin, hydrogen peroxide, purified water

ALCOHOL ANTISEPTIC 80%

TOPICAL SOLUTION

Antiseptic Hand Rub

Non-Sterile Solution

©2020 Gold Eagle Co.

Gold Eagle Co.

4400 S. Kildare

Chicago, IL 60632

(800) 367-3245

MotorForce.com

MADE IN USA

DO NOT AIR SHIP

59001 3.2020